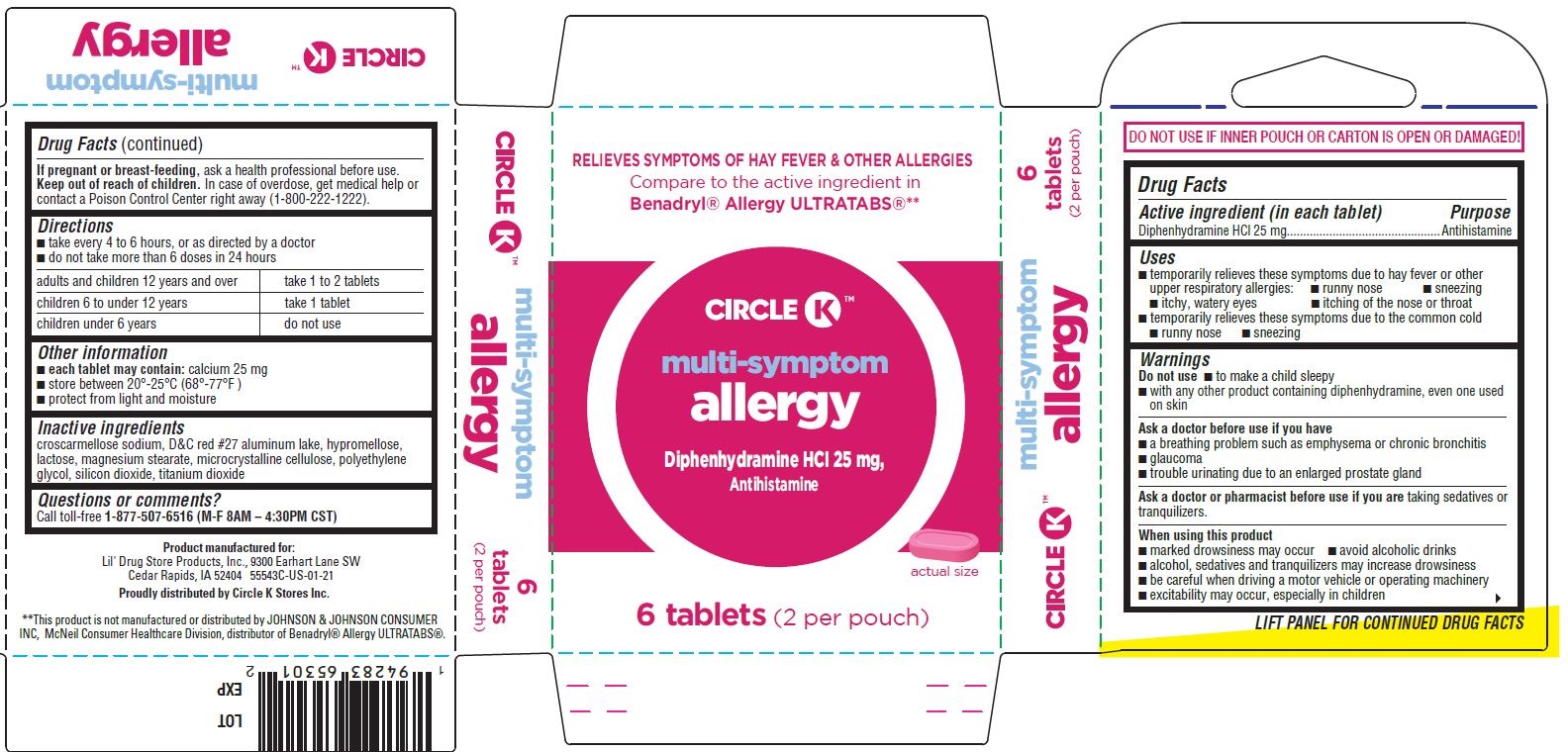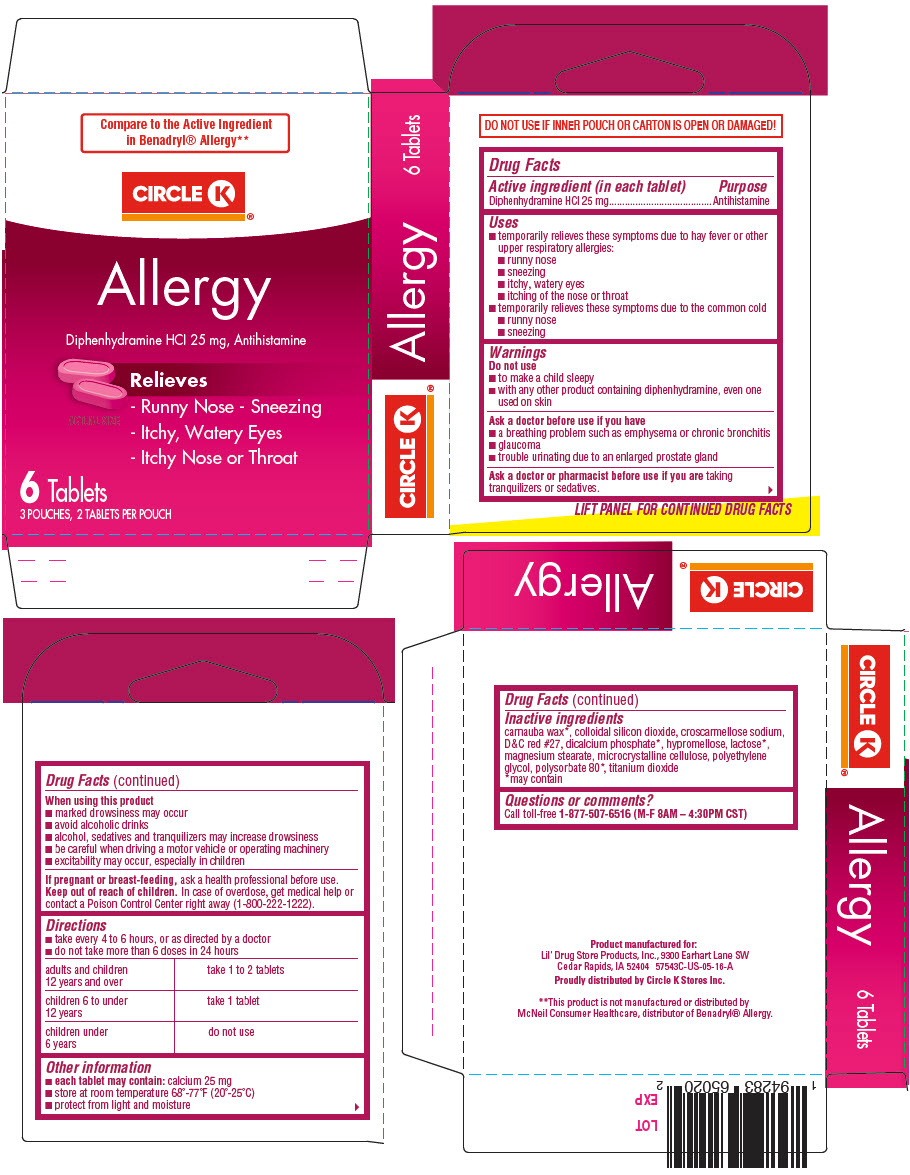 DRUG LABEL: Circle K Allergy
NDC: 66715-5654 | Form: TABLET, FILM COATED
Manufacturer: Lil' Drug Store Products, Inc.
Category: otc | Type: HUMAN OTC DRUG LABEL
Date: 20231214

ACTIVE INGREDIENTS: DIPHENHYDRAMINE HYDROCHLORIDE 25 mg/1 1
INACTIVE INGREDIENTS: CARNAUBA WAX; SILICON DIOXIDE; CROSCARMELLOSE SODIUM; D&C RED NO. 27; ANHYDROUS DIBASIC CALCIUM PHOSPHATE; HYPROMELLOSE, UNSPECIFIED; LACTOSE, UNSPECIFIED FORM; MAGNESIUM STEARATE; MICROCRYSTALLINE CELLULOSE; POLYETHYLENE GLYCOL, UNSPECIFIED; POLYSORBATE 80; TITANIUM DIOXIDE

Circle K™ Allergy
Antihistamine

Drug Facts

Active ingredient (in each tablet)

Diphenhydramine HCl 25 mg

Purpose

Antihistamine

Uses

- temporarily relieves these symptoms due to hay fever or other upper respiratory allergies:
  - runny nose
  - sneezing
  - itchy, watery eyes
  - itching of the nose or throat
- temporarily relieves these symptoms due to the common cold
  - runny nose
  - sneezing

Warnings

Do not use

- to make a child sleepy
- with any other product containing diphenhydramine, even one used on skin

Ask a doctor before use if you have

- a breathing problem such as emphysema or chronic bronchitis
- glaucoma
- trouble urinating due to an enlarged prostate gland

Ask a doctor or pharmacist before use if you are taking tranquilizers or sedatives.

When using this product

- marked drowsiness may occur
- avoid alcoholic drinks
- alcohol, sedatives and tranquilizers may increase drowsiness
- be careful when driving a motor vehicle or operating machinery
- excitability may occur, especially in children

PREGNANCY OR BREAST FEEDING

If pregnant or breast-feeding, ask a health professional before use.

Keep out of reach of children. In case of overdose, get medical help or contact a Poison Control Center right away (1-800-222-1222).

Directions

- take every 4 to 6 hours, or as directed by a doctor
- do not take more than 6 doses in 24 hours

adults and children 12 years and over | take 1 to 2 tablets
children 6 to under 12 years | take 1 tablet
children under 6 years | do not use

Other information

- each tablet may contain: calcium 25 mg
- store at room temperature 68°-77°F (20°-25°C)
- protect from light and moisture

Inactive ingredients

carnauba wax [may contain] , colloidal silicon dioxide, croscarmellose sodium, D&C red #27, dicalcium phosphate , hypromellose, lactose , magnesium stearate, microcrystalline cellulose, polyethylene glycol, polysorbate 80 , titanium dioxide

Questions or comments?

Call toll-free 1-877-507-6516 (M-F 8AM – 4:30PM CST)

Proudly distributed by Circle K Stores Inc.

PRINCIPAL DISPLAY PANEL - 4 Tablet Pouch Carton - NDC 66715-5654-2

Compare to the Active Ingredient
in Benadryl® Allergy**

CIRCLE K™

Allergy

Diphenhydramine HCl 25 mg, Antihistamine

ACTUAL SIZE

Relieves

- Runny Nose - Sneezing
- Itchy, Watery Eyes
- Itchy Nose or Throat

4 Tablets
2 POUCHES, 2 TABLETS PER POUCH

PRINCIPAL DISPLAY PANEL - 6 Tablet Pouch Carton - NDC 66715-5554-3

RELIEVES SYMPTOMS OF HAY FEVER & OTHER ALLERGIES
Compare to the active ingredient in
Benadryl® Allergy ULTRATABS®**

CIRCLE K™

multi-symptom

allergy

Diphenhydramine HCl 25 mg,

Antihistamine

[tablet image]

actual size

6 tablets (2 per pouch)